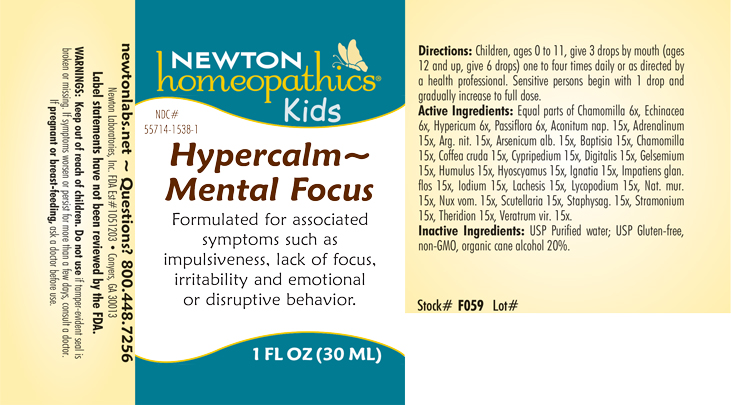 DRUG LABEL: Hypercalm-Mental Focus
NDC: 55714-1538 | Form: LIQUID
Manufacturer: Newton Laboratories, Inc.
Category: homeopathic | Type: HUMAN OTC DRUG LABEL
Date: 20230630

ACTIVE INGREDIENTS: ECHINACEA, UNSPECIFIED 6 [hp_X]/1 mL; GELSEMIUM SEMPERVIRENS ROOT 15 [hp_X]/1 mL; PASSIFLORA INCARNATA FLOWERING TOP 6 [hp_X]/1 mL; ACONITUM NAPELLUS 15 [hp_X]/1 mL; EPINEPHRINE 15 [hp_X]/1 mL; SILVER NITRATE 15 [hp_X]/1 mL; ARSENIC TRIOXIDE 15 [hp_X]/1 mL; BAPTISIA TINCTORIA ROOT 15 [hp_X]/1 mL; MATRICARIA CHAMOMILLA 15 [hp_X]/1 mL; ARABICA COFFEE BEAN 15 [hp_X]/1 mL; CYPRIPEDIUM PARVIFLORUM VAR. PUBESCENS ROOT 15 [hp_X]/1 mL; DIGITALIS 15 [hp_X]/1 mL; HYOSCYAMUS NIGER 15 [hp_X]/1 mL; STRYCHNOS IGNATII SEED 15 [hp_X]/1 mL; IMPATIENS GLANDULIFERA FLOWER 15 [hp_X]/1 mL; IODINE 15 [hp_X]/1 mL; LACHESIS MUTA VENOM 15 [hp_X]/1 mL; LYCOPODIUM CLAVATUM SPORE 15 [hp_X]/1 mL; SODIUM CHLORIDE 15 [hp_X]/1 mL; STRYCHNOS NUX-VOMICA SEED 15 [hp_X]/1 mL; SCUTELLARIA LATERIFLORA WHOLE 15 [hp_X]/1 mL; DELPHINIUM STAPHISAGRIA SEED 15 [hp_X]/1 mL; DATURA STRAMONIUM 15 [hp_X]/1 mL; THERIDION CURASSAVICUM 15 [hp_X]/1 mL; VERATRUM VIRIDE ROOT 15 [hp_X]/1 mL; HOPS 15 [hp_X]/1 mL; HYPERICUM PERFORATUM 6 [hp_X]/1 mL
INACTIVE INGREDIENTS: WATER; ALCOHOL

Hypercalm 1538L

INDICATIONS AND USAGE SECTION

Formulated for associated symptoms such as impulsiveness, lack of focus, irritability and emotional or disruptive behavior.

DOSAGE & ADMINISTRATION SECTION

Directions: Children, ages 0 to 11, give 3 drops by mouth (ages 12 and up, give 6 drops) one to four times daily or a directed by a health professional. Sensitive person begin with 1 drop and gradually increase to full dose.

OTC - ACTIVE INGREDIENT SECTION

Equal parts of Chamomilla 6x, Echinacea 6x, Hypericum perforatum 6x, Passiflora incarnata 6x, Aconitum napellus 15x, Adrenalinum 15x, Argentum nitricum 15x, Arsenicum album 15x, Baptisia tinctoria 15x, Chamomilla 15x, Coffea cruda 15x, Cypripedium pubescens 15x, Digitalis purpurea 15x, Gelsemium sempervirens 15x, Humulus lupulus 15x, Hyoscyamus niger 15x, Ignatia amara 15x, Impatiens glandulifera flos 15x, Iodium 15x, Lachesis mutus 15x, Lycopodium clavatum 15x, Natrum muriaticum 15x, Nux vomica 15x, Scutellaria lateriflora 15x, Staphysagria 15x, Stramonium 15x, Theridion 15x, Veratrum viride 15x.

OTC - PURPOSE SECTION

Formulated for associated symptoms such as impulsiveness, lack of focus, irritability and emotional or disruptive behavior.

INACTIVE INGREDIENT SECTION

USP Purified water; USP Gluten-free, non-GMO, organic cane alcohol 20%

QUESTIONS SECTION

newtonlabs.net – Questions? 800.448.7256

Newton Laboratories, Inc. FDA Est # 1051203 - Conyers, GA 30013

WARNINGS SECTION

WARNINGS: Keep out of reach of children. Do not use if tamper-evident seal is broken or missing. If symptoms worsen or persist for more than a few days, consult a doctor. If pregnant or breast-feeding, ask a doctor before use.

OTC - PREGNANCY OR BREAST FEEDING SECTION

If pregnant or breast-feeding, ask a doctor before use.

OTC - KEEP OUT OF REACH OF CHILDREN SECTION

WARNINGS: Keep out of reach of children.